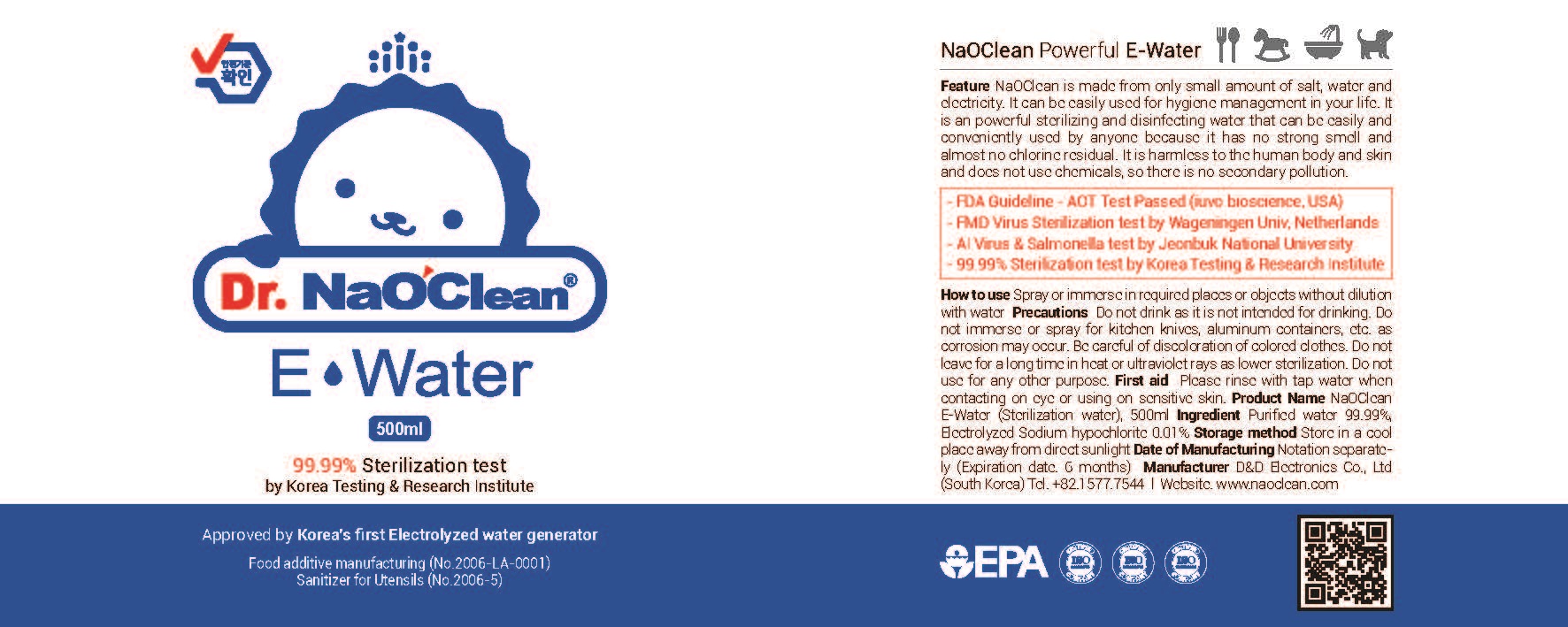 DRUG LABEL: NaOClean E-Water
NDC: 76876-0001 | Form: LIQUID
Manufacturer: D&D Electronics Co Ltd
Category: otc | Type: HUMAN OTC DRUG LABEL
Date: 20200501

ACTIVE INGREDIENTS: SODIUM HYPOCHLORITE 0.01 g/100 mL
INACTIVE INGREDIENTS: WATER

Drug Facts

ACTIVE INGREDIENT

Sodium hypochlorite

PURPOSE

disinfectant

KEEP OUT OF REACH OF THE CHILDREN

INDICATIONS AND USAGE

take appropriate amount to the place or objects

WARNINGS

■ Flammable. Keep away from fire or flame.

■ For external use only.

■ Do not use in eyes.

■ lf swallowed, get medical help promptly.

■ Stop use, ask doctor lf irritation occurs.

■ Keep out of reach of children.

DOSAGE AND ADMINISTRATION

for external use only

INACTIVE INGREDIENT

water